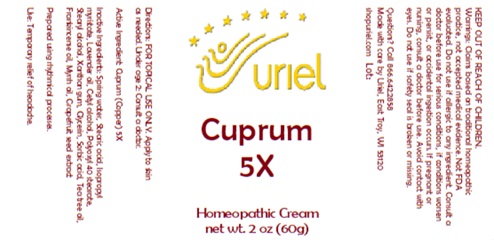 DRUG LABEL: Cuprum 5
NDC: 48951-3138 | Form: CREAM
Manufacturer: Uriel Pharmacy Inc.
Category: homeopathic | Type: HUMAN OTC DRUG LABEL
Date: 20250627

ACTIVE INGREDIENTS: COPPER 5 [hp_X]/1 g
INACTIVE INGREDIENTS: TEA TREE OIL; SORBIC ACID; LAVENDER OIL; WATER; STEARIC ACID; ISOPROPYL MYRISTATE; CETYL ALCOHOL; POLYOXYL 40 STEARATE; STEARYL ALCOHOL; XANTHAN GUM; GLYCERIN; FRANKINCENSE OIL; MYRRH OIL; CITRUS PARADISI SEED

Cuprum 5

INDICATIONS AND USAGE

Directions: FOR TOPICAL USE ONLY.

DOSAGE AND ADMINISTRATION

Apply to skin as needed. Under age 2: Consult a doctor.

Active Ingredient: Cuprum (Copper) 5X

INACTIVE INGREDIENT

Inactive Ingredients: Spring water, Stearic acid, Isopropyl myristate, Lavender oil, Cetyl alcohol, Polyoxyl 40 stearate, Stearyl alcohol, Xanthan gum, Glycerin, Sorbic acid, Tea tree oil, Frankincense oil, Myrrh oil, Grapefruit seed extract

Prepared using rhythmical processes.

PURPOSE

Use: Temporary relief of headache.

KEEP OUT OF REACH OF CHILDREN.

WARNINGS

Warnings: Claims based on traditional homeopathic practice, not accepted medical evidence. Not FDA evaluated. Do not use if allergic to any ingredient. Consult a doctor before use for serious conditions, if conditions worsen or persist, or accidental ingestion occurs. If pregnant or nursing, consult a doctor before use. Avoid contact with eyes. Do not use if safety seal is broken or missing.

Questions? Call 866.642.2858
Made with care by Uriel, East Troy, WI 53120
shopuriel.com Lot: